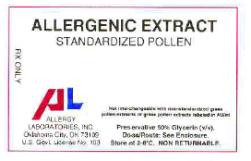 DRUG LABEL: STANDARDIZED BERMUDA GRASS POLLEN
NDC: 54575-084 | Form: INJECTION, SOLUTION
Manufacturer: Allergy Laboratories, Inc.
Category: prescription | Type: HUMAN PRESCRIPTION DRUG LABEL
Date: 20100327

ACTIVE INGREDIENTS: CYNODON DACTYLON POLLEN 10000 [BAU]/1 mL
INACTIVE INGREDIENTS: GLYCERIN 50 mL/100 mL; SODIUM CHLORIDE 0.166 g/100 mL; SODIUM BICARBONATE 0.091 g/100 mL; WATER

Standardized Grasses

ALLERGY LABORATORIES, INC.
Oklahoma City OK 73109

INSTRUCTIONS AND DOSAGE SCHEDULE FOR
STANDARDIZED ALLERGENIC EXTRACTS

BERMUDA GRASS POLLEN (Cynodon dactylon)

KENTUCKY BLUE GRASS POLLEN (Poa pratensis)

MEADOW FESCUE POLLEN (Festuca elatior)

ORCHARD GRASS POLLEN (Dactylis glomerata)

REDTOP GRASS POLLEN (Agrostis alba)

PERENNIAL RYE GRASS POLLEN (Lolium perenne)

SWEET VERNAL GRASS POLLEN (Anthoxanthum odoratum)

TIMOTHY GRASS POLLEN (Phleum pratense)

WARNING

This product is intended for use by physicians who are experienced in the administration of allergenic extracts and the emergency care of anaphylaxis or for use under the guidance of an allergy specialist.

STANDARDIZED GRASS POLLEN EXTRACTS LABELED IN BAU/ml ARE NOT INTERCHANGEABLE WITH GRASS POLLEN EXTRACTS LABELED IN AU/ml OR WITH NON-STANDARDIZED (WEIGHT/VOLUME) GRASS POLLEN EXTRACTS. For guidance in selecting dose, refer to Table A in the Clinical Pharmacology section that describes the potency of non-standardized grass pollen extracts. Comparative skin tests can be performed to determine the relative potency before initial use of new extracts. For previously untreated patents, initial dose must be based on skin testing as described in the Dosage and Administration section of this insert. Patients being switched from other types of extracts to Allergy Laboratories should have their dose adjusted. Extracts standardized in BAU (Bioequivalent Allergy Unit) may differ in potency from non-standardized extracts. Comparative skin tests can be performed to determine relative potency of standardized versus non-standardized extracts. The dosage should be reduced 75% when switching from one lot of standardized grass pollen extract to another Iot. Patients with unstable or severe asthma, including steroid-dependent asthma, are at increased risk for more frequent and more severe reactions from allergy extract injections. Greater caution must be exerted with such patients at all phases of extract administration, but particularly during build up. For example, extract therapy might be initiated at weaker concentrations and built by smaller dosage increments than in comparably allergic rhinitis patients without asthma. Also when asthma is poorly controlled, the injection regimen might be temporarily interrupted (at the discretion of the physician) until control of asthma is re-established. Whenever a reaction occurs in such patients their asthma should be medically stabilized before injections are resumed with an appropriate dosage reduction. Patients should be instructed to recognize adverse reaction symptoms and cautioned to contact physician's office if reaction symptoms occur. As with all allergenic extracts, severe systemic reactions may occur. In certain individuals these life threatening reactions may be fatal. Patients should be observed for at least 30 minutes following treatment and emergency measures as well as personnel trained in their use should be immediately available in the event of a life threatening reaction. Serious adverse reactions can be reported to the U S Food and Drug Administration MedWatch Program. The MedWatch forms can be obtained by calling 1-800-FDA-1088. The address is MedWatch, 5600 Fishers Lane, Rockville, MD 20852-9787.

This product should not be injected intravenously. Subcutaneous injections are recommended.

Patients who are taking non-selective beta blockers may be more reactive to allergens given for testing or treatment and may be unresponsive to the usual doses of epinephrine used to treat allergic reactions. Refer also to the warnings, precautions, adverse reactions and dosage sections below.

DESCRIPTION:

Standardized grass pollen extracts labeled in BAU/ml are not interchangeable with grass pollen extracts labeled in AU/ml or with non-standardized grass pollen extracts. The recommended route of administration for immunotherapy is subcutaneous. The routes of administration for diagnostic purposes are intradermal or prick-puncture of the skin. Do not inject intravenously. The extract is sterile and contains 50% (v/v) glycerin as a preservative. Standardized grass pollen extracts are available in both 10,000 BAU/ml and 100,000 BAU/ml potencies, except for Bermuda which is only available in 10,000 BAU/ml. The source material of the standardized grass extracts are the grass pollens. The 100,000 BAU/ml grass pollen extracts are prepared by extracting pollen at a 1:10 w/v ratio then diluting if necessary to the appropriate range for 100,000 BAU/ml. The 10,000 BAU/ml grass pollen extracts are prepared by dilution of the 100,000 BAU/ml grass pollen extracts. The 10,000 BAU/ml Bermuda grass pollen extract is prepared by extracting Bermuda grass pollen at a 1:10 w/v ratio then diluting if necessary to the appropriate range for 10,000 BAU/ml.

The potency (in Bioequivalent Allergy Units per ml or BAU/ml) of standardized grass pollen extracts is determined by an in-vitro ELISA Competition assay (1) against CBER reference extracts and CBER reference serum pools distributed by the Center for Biologics Evaluation and Research, U S Food and Drug Administration. Potency based on Bioequivalent Allergy Units (BAU/ml) is printed on the label. FDA reference grass pollen extracts were assigned potency designations based on quantitative skin testing (2). The FDA reference extracts which can be diluted 1:500,000 fold intradermally to produce a sum of erythema diameter response of 50mm in highly puncture reactive subjects have been assigned 10,000 BAU/ml. References which can be diluted 1:5,000,000 fold intraderrnally to produce a sum of erythema diameter response of 50mm have been assigned 100,000 BAU/ml.

INACTIVE INGREDIENTS:

Glycerinated extracts contain:

glycerin | 50.0 % v/v
sodium chloride | 0.166 % w/v
sodium bicarbonate | 0.091 % w/v

CLINICAL PHARMACOLOGY:

The allergic state is initiated by an immune response inducing B cells to produce IgE antibodies to specific allergens. IgE antibodies bind to surface receptors on mast cells and basophils. When antigens gain access to the immune system they react with the bound IgE. The reacting antigen to the surface bound IgE stimulates a number of chemical mediators to be released from the mast cells and basophils. These include histamine, Eosinophil Chemotactic Factor (ECF-A) and leukotrienes. These chemical mediators are pharmacologically active at low concentrations and are partially responsible for the biological manifestations of the allergic response. (3)

The mechanism by which immunotherapy achieves hyposensitization is not completely understood. There is an increase in "blocking antibody" (lgG) titer and in some patients a decrease in specific IgE, a decrease in histamine release to specific allergen and an increase in suppressor celI population to specific allergen. These changes may occur only after prolonged therapy. (4)

TABLE A Potency of Commercially Available Allergy Laboratories, Inc. Non-standardized Grass Pollen Extracts (glycerinated 1:20 w/v) In-vitro data by ELISA Competition Assay
 |  | Potency | in | BAU/ml | BAU/ml Range for Equivalence to Reference
GRASS POLLEN EXTRACT |  | Lot #1 |  | Lot #2
Bermuda |  | 14,600 |  | 8,500 |  | 6,999- 14,310
Kentucky Blue |  | 94,000 |  | 150,000 |  | 69,990-143,100
Meadow Fescue |  | 275,000 |  | 105,000 |  | 69,990-143,100
Orchard |  | 96,000 | Not tested |  |  | 69,990-143,100
Redtop |  | 117,000 |  | 58,000 |  | 69,990-143,100
Perennial Rye |  | 195,000 |  | 101,000 |  | 69,990-143,100
Sweel Vernal |  | 67,000 |  | 72,000 |  | 69,990-143,100
Timothy |  | 140,000 |  | 149,000 |  | 69,990-143,100

Clinical data from the Center for Biologics Evaluation and Research is shown in the following tables

TABLE B Puncture and Intradermal Data with CBER Grass Pollen References
1. Puncture Data with 10,000 BAU/ml Grass Pollen Extracts using bifurcated needle
Reference Pollen |  | FDA Lot # |  | N |  | P∑E (mm) Mean Range |  |  |  | P∑W (mm) Mean Range
Bermuda |  | E4-Ber |  | 15 |  | 90.3 |  | 43-123 |  | 15.7 |  | 7-31
June |  | E3-Jkb |  | 15 |  | 77.3 |  | 47-107 |  | 15.9 |  | 6-28
Meadow Fescue |  | E4-MF |  | 15 |  | 81.1 |  | 57-115 |  | 11.9 |  | 7-22
Orchard |  | E4 Or |  | 15 |  | 84.3 |  | 57-111 |  | 14.1 |  | 9-19
Perennial Rye |  | E10-Rye |  | 15 |  | 92.3 |  | 73-135 |  | 17.5 |  | 6.36
Redtop |  | E4-Rt |  | 15 |  | 77.1 |  | 42-98 |  | 14.1 |  | 8-19
Sweel Vernal |  | E4-SV |  | 15 |  | 81.2 |  | 28-123 |  | 15.7 |  | 8-30
Timothy |  | E6-T |  | 15 |  | 88.3 |  | 51-109 |  | 16.9 |  | 8-40
∑E = The sum of the longest diameter of erythema and the orthogonal erythema diameter measured at one half the longest erythema diameter.
∑W = The sum of the longest diameter of wheal and the orthogonal wheal diameter measured at one half the longest wheal diameter.

2. Intradermal Dose of CBER Grass Pollen References for 50mm Sum of Erythema (BAU50)
Reference Pollen |  | FDA Lot # |  |  | BAU50/ml Mean Range
Bermuda |  | E4-Ber |  |  | 0.02 |  | 0.4 – 0.0003
June |  | E3-Jkb |  |  | 0.02 |  | 0.1 – 0.004
Meadow Fescue |  | E4-MF |  |  | 0.02 |  | 0.9 – 0.002
Orchard |  | E4 Or |  |  | 0.02 |  | 1.9 – 0.002
Perennial Rye |  | E10-Rye |  |  | 0.02 |  | 0.7 – 0.002
Redtop |  | E4-Rt |  |  | 0.02 |  | 0.8 – 0.004
Sweel Vernal |  | E4-SV |  |  | 0.02 |  | 1.0 – 0.002
Timothy |  | E6-Ti |  |  | 0.02 |  | 0.6 – 0.002

INDICATIONS AND USAGE:

Standardized grass pollen extracts are used for the diagnosis and treatment of allergic disease to grass pollen. The standardized (Bioequivalent Allergy Unit) extract in these vials is designed primarily for the physician equipped to prepare dilutions and mixtures as required. STANDARDIZED GRASS POLLEN EXTRACTS LABELED IN BAU/ml ARE NOT INTERCHANGEABLE WITH GRASS POLLEN EXTRACTS LABELED IN AU/ml OR WITH NON-STANDARDIZED (WEIGHT/VOLUME) GRASS POLLEN EXTRACTS. Patients being switched from other types of extracts to Allergy Laboratories should have their dose adjusted. Diagnosis of allergic disease to these grasses is made through a combined medical history sufficiently complete to identify allergic symptoms to grass pollen and identification of grass allergy by diagnostic skin testing. It is recommended that diagnostic skin testing (scratch or puncture) be performed with 10,000 BAU/ml grass pollen extracts before testing with 100,000 BAU/ml grass pollen extracts. 10,000 BAU/mL and 100,000 BAU/ml grass pollen extracts for immunotherapy are available for previously treated patients to facilitate dose selection for safe switching from non-standardized to standardized extracts. Patients being treated with grass pollen extracts for the first time can be initially immunized with dilutions prepared from the 10,000 BAU/ml extract (see Dosage and Administration). 100,000 BAU/ml grass pollen extract can be administered if the patient tolerates the 10,000 BAU/ml extract.

Grass pollen immunotherapy is intended for patients whose grass allergic symptoms cannot be satisfactorily controlled by avoidance of the offending allergen or by the use of symptomatic medications. (5)

CONTRAINDICATIONS:

There are no known absolute contraindications to hyposensitization therapy. See precautions section for pregnancy risks.

A patient without a history of grass pollen allergy symptoms and a positive skin test reaction to grass pollen should not be treated. The physician must determine if the benefits outweigh the risks in using these products for treating patients. The benefit to risk ratio should be carefully weighed especially where risks of immunotherapy are higher than usual. This includes severe unstable asthma, highly allergic patients who have had previous severe or unusual problems with injections, pregnancy, or any fragile general medical condition. This also includes patients where potential benefits are limited due to coexisting non-allergic disease such as: non-specific vasomotor rhinitis, nasal septal deviation, nasal polyps, COPD (chronic obstructive pulmonary disease), cardiovascular or other non-allergic respiratory disease.

WARNINGS

See WARNINGS box at the beginning of the instruction sheet.

Extracts standardized using the Bioequivalent Allergy Unit may be more or less potent than extracts based on AU/ml, weight to volume, or PNU methods of expressing potency. See Adverse Reactions section in this insert for a description of the possible local reactions and systemic reactions. Comparative skin tests can be performed to determine the relative potency before initial use of new extracts. DO NOT GIVE ALLERGY INJECTIONS INTRAVENOUSLY. Subcutaneous injections are recommended. Injections may produce large local reactions that may be painful to the patient. DO NOT GIVE FULL-STRENGTH INJECTIONS UNTIL COMPARATIVE SKIN TESTING IS PERFORMED. After inserting the needle, but before injecting extract, withdraw the plunger slightly. If blood appears in the syringe re-insert the needle at another site. Careful selection of dose and injection should prevent most systemic reactions.

PRECAUTIONS:

GENERAL:

The dosage should be reduced 50-75% from the previous dose when starting a patient on a new lot of standardized grass extract from the same manufacturer or from a different manufacturer. Table A in the Clinical Pharmacology section of this insert can be used for guidance when changing from a non-standardized grass extract to a standardized grass extract. The table shows the similarity in potency of two Iots of the non-standardized grass extracts with respect to the 10,000 BAU/ml standardized extracts. Comparative skin testing can be used to determine the dose.

A separate sterile tuberculin type syringe should be used with each patient to prevent cross contamination of extracts. This will also prevent transmission of disease such as hepatitis, AIDS and other infectious diseases. Aseptic technique should always be used when injections of allergenic extracts are administered.

INFORMATION FOR PATIENTS:

Because most serious reactions following the administration of allergenic extracts occur within 30 minutes of the injection, the patient should remain under observation for this period of time. The size of the local reaction should be recorded, because increasingly large local reaction may precede a subsequent systemic reaction with increasing dosage. The patient should be instructed to report any unusual reactions to the attention of the physician. In particular, this includes swelling and/or tenderness at the injection site or reactions such as rhinorrhea, sneezing, coughing, wheezing, shortness of breath, nausea, dizziness or faintness.

DRUG INTERACTIONS:

Patients who are taking non-selective beta blockers may be more reactive to skin tests and may be unresponsive to the usual doses of epinephrine used to treat allergic reactions. Antihistamines can significantly inhibit the immediate skin test reactions. If long acting antihistamines have been taken recently, it is recommended that they should be stopped for the following minimum intervals before skin testing is performed: at least 1 month for astemizole; 1 week for hydroxyzine or cetirizine; 4 to 7 days for Ioratadine; 3 to 4 days for terfenadine or fexofenadine; and 24 to 48 hours for other sustained release antihistamines. (6)

CARCINOGENESIS, MUTAGENESIS, IMPAIRMENT OF FERTILITY:

Long term studies with extracts have not been conducted in animals to determine their potential for carcinogenesis, mutagenesis, or impairment of fertility.

PREGNANCY:

Pregnancy Category C. Animal reproduction studies have not been conducted with allergenic extracts. It is also not known whether allergenic extracts can cause fetal harm when administered to a pregnant woman or can affect reproduction capacity. Allergenic extracts should be given to a pregnant woman only if clearly needed.

Controlled studies of hyposensitization with moderate to high doses of allergenic extracts in pregnant women have failed to demonstrate any risk to the mother or fetus. (7)

Initiation of effective immunotherapy may be beneficial if it allows a pregnant patient to forego medications during the first trimester when the fetus is more vulnerable to teratogenic agents, or if it contributes to better control of asthma so the fetus has less likelihood of being damaged by hypoxemia.

However, with histamines known ability to contract uterine muscles any reaction which would release significant amounts of histamine such as hyposensitization overdose should be avoided. The physician must weigh the benefits of immunotherapy against the risk of anaphylactic reactions that could result in harm to the mother and/or fetus.

Hyposensitization should be used during pregnancy only if clearly necessary and administered cautiously. If a woman is on maintenance dose the occurrence of pregnancy is not an indication to stop injection therapy.

NURSING MOTHERS:

It is not known if allergenic extracts are excreted in human milk. Because many drugs are excreted in human milk, caution should be exercised when extracts are administered to nursing women.

PEDIATRIC USE

Standardized grass pollen extract has not been studied in children, so the safety in children has not been established. The extracts may cause some pain or discomfort when injected, as well as systemic, adverse reactions (see Warnings and Adverse Reactions). The maximum tolerated dose may be less than the adult dose due to the smaller size of the child. Therefore, the volume of the dose may need to be adjusted from the adult schedules provided.

ADVERSE REACTIONS:

(1) Local Reactions:

Some swelling and redness at the site of injection is not unusual. Mild burning that occurs immediately after the injection is normal; this usually subsides in 10 to 20 seconds. If the swelling and redness persist for a period of 24 hours or longer this should be a sign to proceed with caution in increasing the dosage. With the next injection the dosage should remain the same or be decreased. Large local reactions may indicate that a systemic reaction could occur with the next injection if the dosage was increased. If a patient continues to have reactions at the maintenance dose, the patient is considered to have exceeded the maximum tolerated dosage.

(2) Systemic Reactions:

Systemic reactions occur infrequently but must be looked for in all patients, especially highly sensitive patients. Anaphylactic shock and death are always possible, therefore, physicians must be prepared for the treatment of these reactions. Systemic reactions can also be characterized by one or more of the following symptoms: angioedema, tachycardia, conjunctivitis, cough, fainting, hypotension, pallor, rhinitis, urticaria and wheezing.

Systemic reaction can be treated by the immediate application of a tourniquet above the site of injection and the administration of 0.3 to 0.5ml of 1:1000 Epinephrine-Hydrochloride subcutaneously or intramuscularly in the opposite arm. The dosage may be repeated two times at 15 minute intervals. Loosen the tourniquet at least every 10 minutes.

The pediatric dosage for 1:1000 Epinephrine-Hydrochloride is 0.05 to 0.1 ml for infants to 2 years of age; 0.15ml, for children 2 to 6 years; and 0.2ml, for children 6 to 12 years.

Patients should always be observed for at least 30 minutes after any injection. Hypotension can be reversed by using vasopressor agents and volume expanders. Parenteral aminophylline and inhalation bronchodilators may be required for bronchospasm. Oxygen may also be needed. Maintenance of an open airway is critical if upper airway obstruction is present. Adrenal corticosteroids and intravenous antihistamine can be given after adequate epinephrine and circulatory support has been administered. Physicians must be familiar with these systemic reactions and have all the equipment and drugs necessary for proper treatment. (8)

Serious adverse reactions can be reported to the US Food and Drug Administration MedWatch Program. The MedWatch forms can be obtained by calling 1-800-FDA-1088. The address is: MedWatch, 5600 Fishers Lane, Rockville, MD, 20852-9787.

OVERDOSAGE:

Refer to Adverse Reactions section above.

DOSAGE AND ADMINISTRATION:

DIAGNOSTIC SKIN TESTING: These products are used to determine a patient's sensitivity to specific antigens and aid in the diagnosis and treatment of atopic diseases. After a thorough history, a decision can be made as to which allergens will be appropriate to use for testing. The recommended procedure is to initially perform puncture tests, then follow with intradermal tests. For enhanced safety, scratch or puncture test with 10,000 BAU/ml before testing with 100,000 BAU/ml. See recommended dosage below:

SCRATCH OR PUNCTURE TEST: |  | Concentration BAU/ml |  | Dosage
 |  | Bermuda Grass |  | 1 drop
 |  | 10,000
 |  | Other Grasses
 |  | 10,000 |  | 1 drop
 |  | 100,000 |  | 1 drop
INTRADERMAL TEST: |  | Concentration BAU/ml |  | Dosage ml
When scratch or puncture test is negative: |  | 100 |  | 0.02
When scratch or puncture test is positive: |  | [See Table B for information regarding range of BAU/ml that elicits a 50mm response for highly reactive patients. The negative intradermal control used for the 100 BAU/ml concentration should contain 0.5% (v/v) glycerin.] |  | 0.02

FREQUENCY OF ADMINISTRATION:

The number of skin tests applied at one time will depend on the particular patient and their allergic history. These tests should be performed and observed in 15 to 20 minutes. Additional tests may be applied in sequence. Perform tests on the anterolateral aspect of the upper arm on an area that permits the effective application of a tourniquet proximal to the site of the test. The skin at the site of injection should be disinfected with rubbing alcohol before testing.

Puncture testing: Apply one drop of extract to the skin. Pierce the drop of extract and skin using a sterile hypodermic needle or vaccinating needle. Maintain the needle perpendicular to the skin surface and rock the needle back and forth to produce a small hole without bleeding. Do not rotate or gouge the needle. Remove needle from skin and wipe excess extract from skin surface.

Scratch testing: Using a scarifier or needle, make a scratch 1/16 inch long on the epidermis penetrating the outer cornified area but being careful not to draw blood. Apply one drop of extract to the scratch.

Intradermal testing: Use a separate sterile syringe (tuberculin type equipped with a 27 gauge by 3/8 inch needle with intradermal bevel) for each antigen. The tests are made by injecting 0.02ml of allergen into the epidermis. If the test has been performed properly, the solution should raise a bleb 2 to 3mm in diameter. If the bleb does not appear, the injection was made too deeply.

A negative control consisting of the same solution that the extract was prepared in, should be applied to one of the sites in the same manner as the tests being performed. For example, the negative intradermal control should contain 0.5% (v/v) glycerin, if a 100 BAU/ml concentration grass is used for intradermal testing. Histamine phosphate should be used as a positive control for evaluation of skin testing. Histamine phosphate is available from other manufacturers. See their directions for use, for recommended dosage and interpretation of results.

A positive reaction usually develops in 15 to 20 minutes. The positive response is a wheal and flare reaction that is larger than the negative control and judged on the size of the reaction. Scratch or puncture tests may not elicit as large and well defined reaction as the intradermal. (5)

The following grading system for intradermal testing is recommended (9):

 | Reaction | Erythema | Wheal
 | 0 | <5mm | <5mm
 | +/- | 5-10mm | 5-10mm
 | 1+ | 11-20mm | 5-10mm
 | 2+ | 21-30mm | 5-10mm
 | 3+ | 31-40mm | 10-15mm or with pseudopods
 | 4+ | >40mm | >15mm or with many pseudopods

IMMUNOTHERAPY:

The following are two methods of injection therapy:

1. Pre-seasonal in which treatment is begun three months before seasonal difficulty begins and brought to maintenance dose by injections 4 to 7 days apart and discontinued after that season ends.

2. Perennial treatment is the recommended mode of therapy in which the patient is, by injection therapy, brought up to tolerated maintenance dose and remains at that dose until amelioration of allergic symptoms occurs. Injections may be given at intervals of 4 to 7 days.

Allergenic extracts must be diluted before use. Normally immunotherapy can be started with a 1 BAU/ml dilution. If a patient appears to be extremely sensitive, based on skin testing results, dilutions of the extract can further be made before injections are started. See Table B for additional information. The following are suggested procedures for making a proper dilution series. Recommended diluents contain 0.9% sodium chloride and 0.4% phenol as a preservative. Dlluents with HSA (Human Serum Albumin) as a stabilizer can also be used. Allergenic extracts should be inspected visually for particulate matter and discoloration prior to administration, whenever solution and container permit.

TEN FOLD DILUTION SERIES:
EXTRACT VOLUME | EXTRACT CONCENTRATION BAU/ml | DILUENT VOLUME | DILUTION CONCENTRATION BAU/ml
1 part | 100,000 + | 9 parts = | 10,000
1 part | 10,000 + | 9 parts = | 1,000
1 part | 1,000 + | 9 parts = | 100
1 part | 100 + | 9 parts = | 10
1 part | 10 + | 9 parts = | 1

Perennial treatment may be started using the following dosage and dilution schedule. (Modified from Reference 10) This schedule is only illustrative and may not be applicable to all patients, since the degree of sensitivity to grass allergens differs among individuals. The dose administered must be adjusted based on the patient's sensitivity and tolerance. Initial dose can be based on end point titration using a dose that elicits a 1-2+ reaction. Maintenance dose is based on patient tolerance.

Dose # | Dose Volume (ml) | Concentration
1 | 0.05 | 1 BAU/ml
2 | 0.10
3 | 0.20
4 | 0.30
5 | 0.40
6 | 0.50
7 | 0.05 | 10 BAU/ml
8 | 0.10
9 | 0.20
10 | 0.30
11 | 0.40
12 | 0.50
13 | 0.05 | 100 BAU/ml
14 | 0.10
15 | 0.20
16 | 0.30
17 | 0.40
18 | 0.50
19 | 0.05 | 1,000 BAU/ml
20 | 0.10
21 | 0.20
22 | 0.30
23 | 0.40
24 | 0.50
25 | 0.05 | 10,000 BAU/ml
26 | 0.10
27 | 0.20
28 | 0.30
29 | 0.40
30 | 0.50
31 | 0.05 | 100,000 BAU/ml
32 | 0.10
33 | 0.20
34 | 0.30
35 | 0.40

Gradually increase the dose as outlined in the schedule. If you give a dose that causes a mild local reaction (manifested by warmth or redness) repeat the same dose. If the reaction is severe or systemic (manifested as hives, asthma, or hay fever) drop back a dose in schedule and build again. If a severe local reaction or a systemic reaction is again encountered, this should be considered more than the maximum tolerance for this patient. The maintenance dose is the largest dose that relieves symptoms without producing local reactions. The size and interval of doses will vary and can be adjusted as necessary. The normal interval between doses is 4 to 7 days. The usual duration of treatment has not been established. A period of two or three years of injection therapy constitutes an average minimum course of treatment.

HOW SUPPLIED:

Bulk extract (stock concentrate) in 50% (v/v) glycerin containing 10,000 BAU/ml or 100,000 BAU/ml is supplied in 10ml, 30ml, and 50ml vials. Bermuda Grass bulk extract is available in 10,000 BAU/ml only. Scratch testing for Bermuda Grass in 50% (v/v) glycerin containing 10,000 BAU/ml is supplied in 2ml dropper vials. Scratch testing for the other grasses in 50% (v/v) glycerin containing 10,000 BAU/ml or 100,000 BAU/ml is supplied in 2ml dropper vials. Intradermal testing (aqueous) for all standardized grasses containing 100 BAU/ml is supplied in 5ml vials.

STORAGE:

These extracts should be stored at 2 to 8 degrees Celsius. Excessive heating (above room temperature) and repeated freeze-thawing should be avoided. The dating period (expiration date) is shown on the vial label. Once extracts are diluted the shelf life decreases. Extracts should be reordered when out of date. Please allow a minimum of three (3) weeks for delivery due to the holding period for sterility testing.

REFERENCES:

1. ELISA Competition Assay, October 1993. In Methods of the Allergenics Products Testing Laboratory, Food and Drug Administration.
2. Turkeltaub, P. Rastogi, S.C.: Quantitative Intradermal Procedure for Evaluation of Subject Sensitivity to Standardized Allergenic Extracts and for Assignment of Bioequivalent Allergy Units to Reference Preparations Using the ID5oEAL Method, November 1994. In Methods of the Allergenic Products Testing Laboratory Center for Biologics Evaluation and Research, Food and Drug Administration.
3. Wasserman, S.I.: Biochemical Mediators of Allergic Reactions. In Patterson, R (ed): Allergic Diseases: Diagnosis and Management, p. 86, Philadelphia, J.B. Lippincott Co., 1985.
4. Grammer, L.C.: Principle of Immunologic Management of Allergic Diseases Due to Extrinsic Antigens. In Patterson, R. (ed) Allergic Diseases: Diagnosis and Management, p. 358, Philadelphia, J.B. Lippincoit Co., 1985.
5. Booth, B.H., Diagnosis of Immediate Hypersensitivity, In Patterson, R. (ed): Allergic Diseases: Diagnosis and Management, p. 102, Philadelphia, J.B. Lippincott Co., 1985.
6. Bousquet, J., Michel F.: In vivo Methods for Study of Allergy: Skin Tests, Techniques, and Interpretation. In Middleton, E. Jr., Reed, C.E. and Ellis, E.F. (ed): Allergy Principles and Practice, (Vol. 1) p. 583, St Louis. The C.V. Mosby Co., 1993.
7. Metzger, W.J. et. al.: The Safety of Immunotherapy During Pregnancy. J. Allergy Clin. Immunol., 64 (4): 268-272, 1978.
8. Patterson, R. et. al.: Immunotherapy. In Middleton, E. Jr., Reed, C.E. and Ellis, E.F. (ed): Allergy; Principles and Practice, (Vol. 2) p. 1119, St Louis, The C.V. Mosby Co., 1983.
9. Norman, P.S., In vivo Methods of Study of Allergy: Skin and Mucosal Tests, Techniques and Interpretation. In Middleton, E. Jr. Reed, C.E. and Ellis, E.F. (ed): Allergy Principles and Practice, (Vol. 1) p. 258, St Louis, The C.V. Mosby Co., 1978.
10. Van Metre, T.E. Jr, Adkinson, N.F. Jr.: Immunotherapy for Aeroallergen Disease. In Middleton, E. Jr., Reed, C.E. and Ellis, E.F. (ed): Allergy Principles and Practice, (Vol. 2) p. 1499, St Louis, The C.V. Mosby Co. 1993.

Revised 5/20/97

ALLERGY LABORATORIES, INC.
U.S. License #103
Oklahoma City, OK 73109 • (405) 235-1451 • (800) 654-3971

PRINCIPAL DISPLAY PANEL

ALLERGENIC EXTRACT

STANDARDIZED POLLEN

Preservative 50% Glycerin (v/v)

Dose/Route: See Enclosure

Store at 2-8°C, NON RETURNABLE

ALLERGY

LABORATORIES, INC

Oklahoma City, OK 73109

U.S Govt. License No. 103